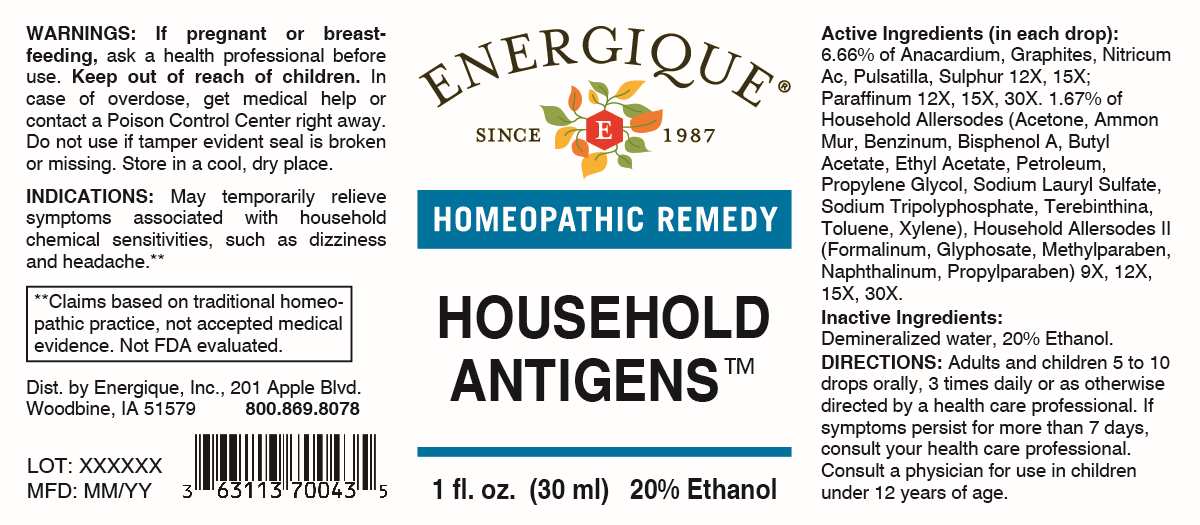 DRUG LABEL: Household Antigens
NDC: 44911-0725 | Form: LIQUID
Manufacturer: Energique, Inc.
Category: homeopathic | Type: HUMAN OTC DRUG LABEL
Date: 20241220

ACTIVE INGREDIENTS: ACETONE 9 [hp_X]/1 mL; SODIUM TRIPOLYPHOSPHATE, UNSPECIFIED FORM 9 [hp_X]/1 mL; PROPYLENE GLYCOL 9 [hp_X]/1 mL; BENZENE 9 [hp_X]/1 mL; AMMONIUM CHLORIDE 9 [hp_X]/1 mL; SODIUM LAURYL SULFATE 9 [hp_X]/1 mL; TURPENTINE OIL 9 [hp_X]/1 mL; BUTYL ACETATE 9 [hp_X]/1 mL; ETHYL ACETATE 9 [hp_X]/1 mL; TOLUENE 9 [hp_X]/1 mL; XYLENE (MIXED ISOMERS) 9 [hp_X]/1 mL; BISPHENOL A 9 [hp_X]/1 mL; KEROSENE 9 [hp_X]/1 mL; FORMALDEHYDE SOLUTION 9 [hp_X]/1 mL; GLYPHOSATE 9 [hp_X]/1 mL; METHYLPARABEN 9 [hp_X]/1 mL; NAPHTHALENE 9 [hp_X]/1 mL; PROPYLPARABEN 9 [hp_X]/1 mL; SEMECARPUS ANACARDIUM JUICE 12 [hp_X]/1 mL; GRAPHITE 12 [hp_X]/1 mL; NITRIC ACID 12 [hp_X]/1 mL; PULSATILLA PRATENSIS WHOLE 12 [hp_X]/1 mL; SULFUR 12 [hp_X]/1 mL; PARAFFIN 12 [hp_X]/1 mL
INACTIVE INGREDIENTS: WATER; ALCOHOL

DRUG FACTS:

ACTIVE INGREDIENTS:

(in each drop): 6.66% of Anacardium Orientale, Graphites, Nitricum Acidum, Pulsatilla, Sulphur 12X, 15X; Paraffinum 12X, 15X, 30X. 1.67% of Household Allersodes (Acetone, Ammonium Muriaticum, Benzinum, Bisphenol A, Butyl Acetate, Ethyl Acetate, Petroleum, Propylene Glycol, Sodium Lauryl Sulfate, Sodium Tripolyphosphate, Terebinthina, Toluene, Xylene), Household Allersodes II (Formalinum, Glyphosate, Methylparaben, Naphthalinum, Propylparaben), 9X, 12X, 15X, 30X.

PURPOSE:

May temporarily relieve symptoms associated with household chemicals sensitivities, such as dizziness and headache.**

**Claims based on traditional homeopathic practice, not accepted medical evidence. Not FDA evaluated.

WARNINGS:

If pregnant or breast-feeding, ask a health professional before use.

Keep out of reach of children. In case of overdose, get medical help or contact a Poison Control Center right away.

Do not use if tamper evident seal is broken or missing.

Store in a cool, dry place.

KEEP OUT OF REACH OF CHILDREN:

In case of overdose, get medical help or contact a Poison Control Center right away.

DIRECTIONS:

Adults and children 5 to 10 drops orally, 3 times daily or as otherwise directed by a health care professional. If symptoms persist for more than 7 days, consult your health care professional. Consult a physician for use in children under 12 years of age.

INDICATIONS:

May temporarily relieve symptoms associated with household chemicals sensitivities, such as dizziness and headache.**

**Claims based on traditional homeopathic practice, not accepted medical evidence. Not FDA evaluated.

INACTIVE INGREDIENTS:

Demineralized water, 20% Ethanol.

QUESTIONS:

Dist. by Energique, Inc.

201 Apple Blvd

Woodbine, IA 51579

800-869-8078

PACKAGE LABEL DISPLAY:

ENERGIQUE

since 1987

HOMEOPATHIC REMEDY

HOUSEHOLD ANTIGENS

1 fl. oz (30 ml)